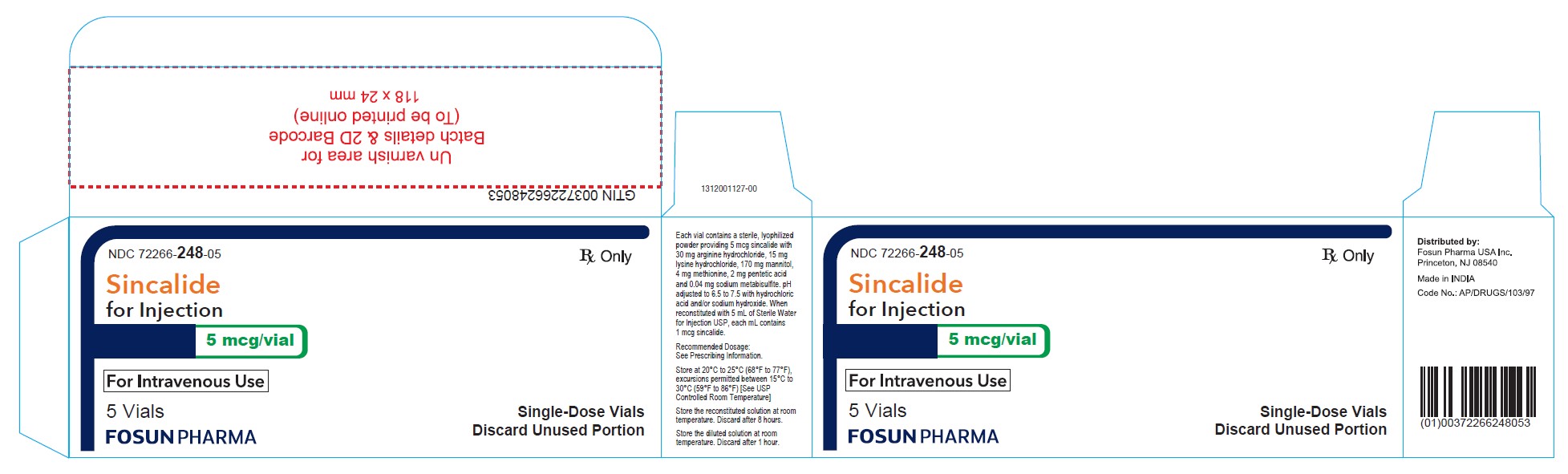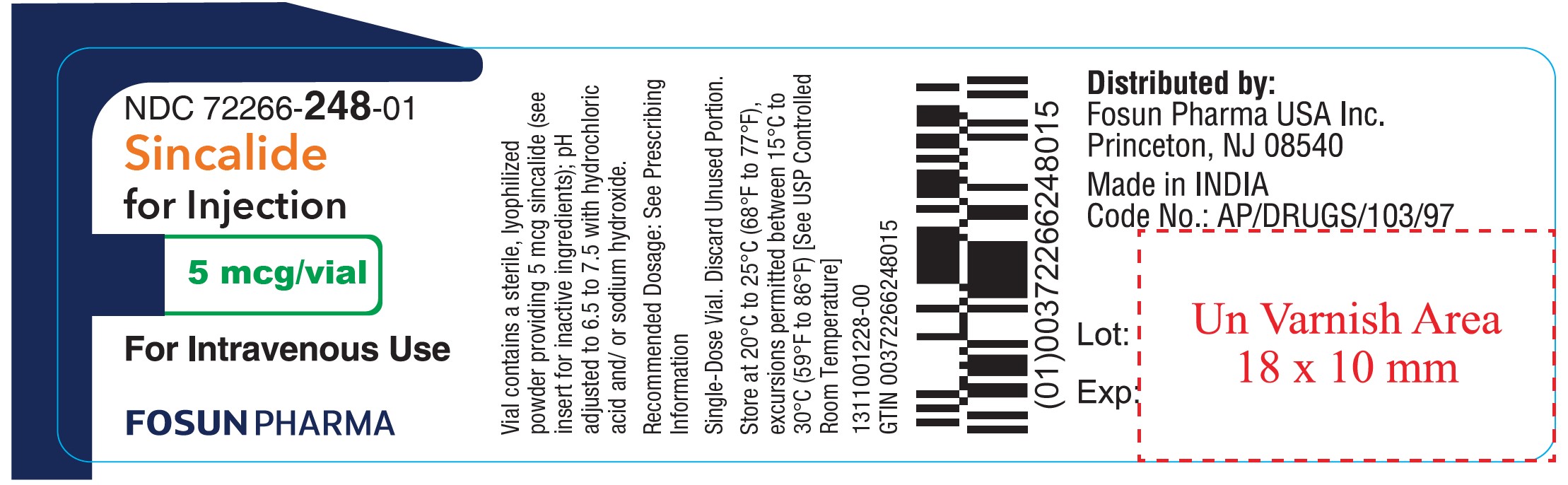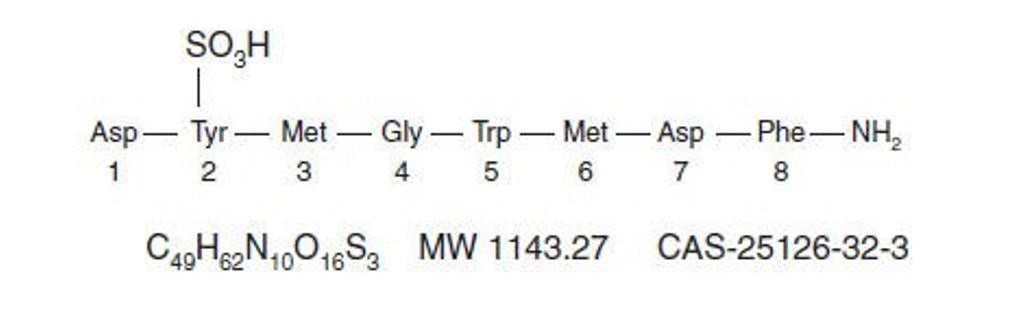 DRUG LABEL: Sincalide
NDC: 72266-248 | Form: INJECTION, POWDER, LYOPHILIZED, FOR SOLUTION
Manufacturer: FOSUN PHARMA USA INC
Category: prescription | Type: HUMAN PRESCRIPTION DRUG LABEL
Date: 20240514

ACTIVE INGREDIENTS: SINCALIDE 5 ug/5 mL
INACTIVE INGREDIENTS: MANNITOL 170 mg/5 mL; ARGININE HYDROCHLORIDE 30 mg/5 mL; LYSINE HYDROCHLORIDE 15 mg/5 mL; METHIONINE 4 mg/5 mL; PENTETIC ACID 2 mg/5 mL; SODIUM METABISULFITE 0.04 mg/5 mL

HIGHLIGHTS OF PRESCRIBING INFORMATION

These highlights do not include all the information needed to use SINCALIDE FOR INJECTION safely and effectively. See full prescribing information for SINCALIDE FOR INJECTION
SINCALIDE for injection, for intravenous use
Initial U.S. Approval: 1976

RECENT MAJOR CHANGES

Contraindications (4) 10/2023
Warnings and Precautions, Anaphylaxis, Anaphylactic Shock and other Serious Hypersensitvity Reactions (5.1) 10/2023

1 INDICATIONS AND USAGE

Sincalide for Injection is a cholecystokinin (CCK) analog indicated in adults to:

- stimulate gallbladder contraction, as may be assessed by various methods of diagnostic imaging, or to obtain by duodenal aspiration a sample of concentrated bile for analysis of cholesterol, bile salts, phospholipids, and crystals. (1)

- stimulate pancreatic secretion in combination with secretin prior to obtaining a duodenal aspirate for analysis of enzyme activity, composition, and cytology. (1)

- accelerate the transit of a barium meal through the small bowel, thereby decreasing the time and extent of radiation associated with fluoroscopy and x-ray examination of the intestinal tract. (1)

2 DOSAGE AND ADMINISTRATION

Recommended Adult Dosage and Administration by Indication:

To Stimulate Contraction of the Gallbladder

- 0.02 mcg/kg as a single dose over 30 to 60 seconds via intravenous injection. If satisfactory contraction does not occur in 15 minutes, administer a dose of 0.04 mcg/kg over 30 to 60 seconds. (2.1)
- Alternatively consider an intravenous infusion to reduce gastrointestinal adverse reactions: 0.12 mcg/kg diluted in 100 mL of 0.9% Sodium Chloride Injection USP and infused over 50 minutes at a rate of 2 mL per minute. (2.1, 2.2, 5.3)

To Stimulate Pancreatic Secretion in Combination with Secretin

- 30 minutes after initiation of secretin for injection, administer 0.02 mcg/kg diluted in 30 mL of 0.9% Sodium Chloride Injection USP and infused over 30 minutes at a rate of 1 mL per minute. (2.1, 2.2)

To Accelerate Transit of a Barium Meal Through the Small Intestine:

- After the barium meal is beyond the proximal jejunum, administer 0.04 mcg/kg over 30 to 60 seconds via intravenous injection. (2.1)
- If satisfactory transit of the barium meal has not occurred in 30 minutes, administer a second dose of 0.04 mcg/kg over 30 to 60 seconds. (2.1)
- Alternatively consider an intravenous infusion to reduce gastrointestinal adverse reactions: 0.12 mcg/kg diluted in 100 mL 0.9% Sodium Chloride Injection USP and infused over 30 minutes. (2.1, 2.2, 5.3)

3 DOSAGE FORMS AND STRENGTHS

For injection: 5 mcg of sincalide as a lyophilized cake or powder in a single-dose vial for reconstitution (3)

4 CONTRAINDICATIONS

- History of hypersensitivity to sulfites or sincalide. (4, 5.1)
- Intestinal obstruction. (4)

5 WARNINGS AND PRECAUTIONS

- Anaphylaxis, Anaphylactic Shock and Other Serious Hypersensitivity Reactions: Contains sodium metabisulfite. Serious reactions may occur during or soon after administration. If symptoms occur, discontinue the drug. (4, 5.1)
- Evacuation of Gallstones: Stimulation of gallbladder contraction in patients with small gallbladder stones could lead to the evacuation of the stones from the gallbladder, resulting in their lodging in the cystic duct or in the common bile duct. (5.2)
- Gastrointestinal Adverse Reactions with Intravenous Injection: Administration as an intravenous injection may cause transient nausea, vomiting, abdominal pain or cramping, dizziness or flushing. To reduce the risk of adverse reactions when used to simulate contraction of the gallbladder or accelerate transit of a barium meal through the small intestine, administer as an intravenous infusion over 50 or 30 minutes, respectively. (2.1, 5.3)
- Preterm Labor or Spontaneous Abortion: Advise pregnant women of the potential risk for preterm labor and spontaneous abortion. (5.4, 8.1)

6 ADVERSE REACTIONS

Most common adverse reactions (≥20%) are: abdominal discomfort or pain, and nausea. (6)

To report SUSPECTED ADVERSE REACTIONS, contact Fosun Pharma USA Inc. at 1-866-611-3762 or FDA at 1-800-FDA-1088 or www.fda.gov/medwatch.

7 DRUG INTERACTIONS

Drugs that Affect Gallbladder Motility or Contractile Response: May interfere with response to sincalide. Consider discontinuing these drugs prior to administration of Sincalide for Injection, when used to stimulate contraction of the gallbladder. (7.1)

FULL PRESCRIBING INFORMATION

1 INDICATIONS AND USAGE

Sincalide for Injection is indicated in adults to:

- stimulate gallbladder contraction, as may be assessed by various methods of diagnostic imaging, or to obtain by duodenal aspiration a sample of concentrated bile for analysis of cholesterol, bile salts, phospholipids, and crystals;
- stimulate pancreatic secretion in combination with secretin prior to obtaining a duodenal aspirate for analysis of enzyme activity, composition, and cytology;
- accelerate the transit of a barium meal through the small bowel, thereby decreasing the time and extent of radiation associated with fluoroscopy and x-ray examination of the intestinal tract.

2 DOSAGE AND ADMINISTRATION

2.1 Recommended Dosage and Administration Instructions

The recommended dosage and administration of Sincalide for Injection by indication is shown in Table 1. For preparation instructions see Dosage and Administration (2.2).

Table 1: Recommended Adult Dosage and Administration of Sincalide for Injection by Treatment Indication
To stimulate contraction of the gallbladder | Sincalide for Injection 0.02 mcg/kg as a single dose over 30 to 60 seconds via intravenous injection. If satisfactory contraction does not occur in 15 minutes, administer a dose of 0.04 mcg/kg over 30 to 60 seconds.; Alternatively, Consider an Intravenous Infusion to Reduce Gastrointestinal Adverse Reactions [see Warnings and Precautions (5.3)]: 0.12 mcg/kg diluted in 100 mL of 0.9% Sodium Chloride Injection USP and infused over 50 minutes at a rate of 2 mL per minute
To stimulate pancreatic secretion in combination with secretin for injection | Secretin for Injection: 0.25 units/kg as intravenous infusion over 60 minutes; Sincalide for Injection: 30 minutes after initiation of secretin infusion, administer Sincalide for Injection 0.02 mcg/kg diluted in 30 mL of 0.9% Sodium Chloride Injection USP and infused over 30 minutes at a rate of 1 mL per minute.
To accelerate the transit of a barium meal through the small intestine | After the barium meal is beyond the proximal jejunum, administer Sincalide for Injection 0.04 mcg/kg over 30 to 60 seconds via intravenous injection.; If satisfactory transit of the barium meal has not occurred in 30 minutes, administer a second dose of 0.04 mcg/kg over 30 to 60 seconds.; Alternatively, Consider an Intravenous Infusion to Reduce Gastrointestinal Adverse Reactions[See Warnings and Precautions (5.3)]: 0.12 mcg/kg diluted in 100 mL 0.9% Sodium Chloride Injection USP and infused over 30 minutes.

2.2 Preparation Instructions

For Intravenous Injection

- Reconstitute Sincalide for Injection aseptically by adding 5 mL of Sterile Water for Injection USP to the vial.
- Inspect the reconstituted solution visually for particulate matter and discoloration after reconstitution and prior to administration.
- Withdraw the prescribed dose of the reconstituted solution from the vial and administer as an intravenous injection over 30 to 60 seconds, as shown in Table 1. Discard the unused portion.
- Store the reconstituted solution at room temperature. Discard after 8 hours.
- For single use only; discard unused portion.

For Intravenous Infusion

- Reconstitute Sincalide for Injection aseptically by adding 5 mL of Sterile Water for Injection USP to the vial.
- After reconstitution, withdraw the prescribed dose of the solution from the vial. Discard unused portion.
- Dilute the reconstituted solution in 30 mL or 100 mL of 0.9% Sodium Chloride Injection USP, depending on the indication, as described in Table 1.
- Inspect the Sincalide solutions visually for particulate matter and discoloration after reconstitution, dilution and prior to administration.
- Store the diluted solution at room temperature. Discard after 1 hour

3 DOSAGE FORMS AND STRENGTHS

For injection: 5 mcg of sincalide as a lyophilized white to off-white cake or powder for reconstitution in a single-dose vial.

4 CONTRAINDICATIONS

Sincalide for Injection is contraindicated in patients with:

- a history of a hypersensitivity reaction to sulfites or sincalide. Serious hypersensitivity reactions have included anaphylaxis and anaphylactic shock [see Warnings and Precautions (5.1), Adverse Reactions (6)].
- intestinal obstruction.

5 WARNINGS AND PRECAUTIONS

5.1 Anaphylaxis, Anaphylactic Shock and Other Serious Hypersensitivity Reactions

Contains sodium metabisulfite [see Description (11)], a sulfite that may cause allergic-type reactions including anaphylactic symptoms and life-threatening or less severe asthmatic episodes in certain susceptible people. The overall prevalence of sulfite sensitivity in the general population is unknown and probably low. Sulfite sensitivity is seen more frequently in asthmatic than in nonasthmatic people.

In postmarketing experience, anaphylaxis, anaphylactic shock and other serious hypersensitivity reactions have been reported during and within one hour following administration of sincalide [see Adverse Reactions (6)].

Sincalide for Injection is contraindicated in patients with a history of hypersensitivity to sulfites. Due to the potential for anaphylaxis, appropriate medical support should be readily available when Sincalide for Injection is administered. If anaphylaxis or other hypersensitivity reactions occur, immediately discontinue the infusion and initiate appropriate medical treatment. Observe patients closely during and after the infusion. Do not reinitiate Sincalide for Injection in patients who have experienced symptoms of hypersensitivity [see Contraindications (4)].

5.2 Evacuation of Gallstones

Stimulation of gallbladder contraction in patients with small gallbladder stones could lead to the evacuation of the stones from the gallbladder, resulting in their lodging in the cystic duct or in the common bile duct.

5.3 Gastrointestinal Adverse Reactions with Intravenous Injection

Administration of Sincalide for Injection as an intravenous injection may cause adverse reactions such as nausea, vomiting, abdominal pain or cramping, dizziness, and flushing [see Adverse Reactions (6)]. These reactions are generally transient. To reduce the risk of adverse reactions with intravenous injection when used to simulate contraction of the gallbladder or accelerate transit of a barium meal through the small intestine, administer Sincalide for Injection as an intravenous infusion over 50 or 30 minutes, respectively [see Dosage and Administration (2.1)].

5.4 Preterm Labor or Spontaneous Abortion

Based on limited human data and mechanism of action, advise pregnant patients that Sincalide for Injection may cause preterm labor or spontaneous abortion [see Use in Specific Populations (8.1)].

6 ADVERSE REACTIONS

The following clinically significant adverse reactions are described elsewhere in labeling:

- Anaphylaxis, anaphylactic shock, and other serious hypersensitivity reactions [see Warnings and Precautions (5.1)]
- Evacuation of gallstones [see Warnings and Precautions (5.2)]
- Adverse reactions with intravenous injection [see Warnings and Precautions (5.3)]
- Preterm labor or spontaneous abortion [see Warnings and Precautions (5.4)]

The following adverse reactions associated with the use of sincalide were identified in clinical trials or postmarketing reports. Because these reactions were reported voluntarily from a population of uncertain size, it is not always possible to estimate their frequency, reliably, or to establish a causal relationship to drug exposure.

The most frequent adverse reactions (20% or greater) are gastrointestinal: abdominal discomfort or pain, and nausea; these may not necessarily indicate an abnormality of the biliary tract unless there is other clinical or radiologic evidence of disease.

Less common adverse reactions include:

Hypersensitivity reactions: anaphylaxis and anaphylactic shock, hypotension, throat tightness, bradycardia, shortness of breath, nausea, abdominal cramping, diaphoresis, hives, rash, itching; and numbness of face, lips and eyes [see Contraindications (4)].

Neurological reactions: seizures, headache.

Vasovagal reactions: dizziness, loss of consciousness, nausea, diaphoresis, syncope and hypotension (generally self-limiting).

Other: nausea, vomiting, flushing, hypertension, urge to defecate, diarrhea, sneezing.

7 DRUG INTERACTIONS

7.1 Drugs that Affect Gallbladder Motility or Contractile Response

Drugs that may stimulate or inhibit gallbladder motility or contractile response, may interfere with the response to sincalide. Consider discontinuing these drugs prior to administration of Sincalide for Injection, when used to simulate contraction of the gallbladder.

8 USE IN SPECIFIC POPULATIONS

8.1 Pregnancy

Risk Summary

Based on limited human data and mechanism of action, Sincalide for Injection may cause preterm labor or spontaneous abortion [see Warnings and Precautions (5.4)]. Limited available data with Sincalide for Injection are insufficient to inform a drug-associated risk of adverse developmental outcomes. In animal embryo-fetal development studies in which sincalide was administered to hamsters and rats during the period of organogenesis, no effects were seen at doses comparable to the maximum recommended clinical dose on a mg/kg basis. However, in a prenatal development study in which rats were administered sincalide during organogenesis through parturition, decreased weight gain and developmental delays were observed at a dose 122 times higher than the maximum recommended human dose based on body surface area.

The estimated background risk of major birth defects and miscarriage for the indicated population is unknown. All pregnancies have a background risk of birth defect, loss, or other adverse outcomes. In the U.S. general population, the estimated background risk of major birth defects and miscarriage in clinically recognized pregnancies is 2 to 4% and 15 to 20%, respectively.

Data

Animal Data

There were no effects on embryo-fetal development in hamsters when sincalide was administered subcutaneously at 250 or 750 ng/kg during organogenesis (Gestation Days 7 to 13) at doses up to 0.8 times the maximum recommended dose of 120 ng/kg on a body surface area basis. No effects on embryo-fetal development were observed in Sprague-Dawley rats at subcutaneous doses of 250, 450, or 750 ng/kg from Gestation Days 6 to16, representing 1.0 time the maximum recommended human dose on a body surface area basis. In a separate study at a higher dose of 90 mcg/kg administered subcutaneously to CFY rats from Gestation Day 10 through parturition (representing 122 times the maximum recommended human dose on a body surface area basis), offspring showed decreased growth, behavioral changes, and developmental delays.

8.2 Lactation

Risk Summary

There are no data regarding the presence of sincalide in human or animal milk, the effects on the breastfed infant, or the effects on milk production. The developmental and health benefits of breastfeeding should be considered along with the mother’s clinical need for Sincalide for Injection and any potential adverse effect on the breastfed infant from Sincalide for Injection or from the underlying condition.

8.4 Pediatric Use

The safety and effectiveness in pediatric patients have not been established.

Animal Data

Direct injection of sincalide in neonatal rats reduced milk consumption with the youngest rats exhibiting the greatest sensitivity to this effect. Although safety margins relative to maternal doses cannot be calculated since rat pups were injected directly, the safety margin in the youngest rat pups was less than 0.1 on a body surface area bases compared to the maximum adult clinical dose. At higher doses administered subcutaneously in neonatal rats, transient behavioral changes and small effects on physical developmental milestones such as ear opening, eye opening, and incisor appearance were observed (at doses 10 to 200-fold higher than the maximum recommended human dose on a body surface area basis).

8.5 Geriatric Use

Clinical studies of sincalide did not include sufficient numbers of subjects aged 65 and over to determine whether they respond differently from younger subjects.

10 OVERDOSAGE

In the event of an overdose, symptoms related to vagal stimulation, such as gastrointestinal symptoms (abdominal cramps, nausea, vomiting and diarrhea), hypotension with dizziness or fainting may occur. Overdosage symptoms should be treated symptomatically and should be of short duration.

A single bolus intravenous injection of 0.05 mcg/kg (approximately 2 to 3 times the human dose of 0.02 mcg/kg), sincalide caused hypotension and bradycardia in dogs. In addition, higher doses injected intravenously once or repeatedly in dogs caused syncope and ECG changes (approximately 5 times the human dose of 0.02 mcg/kg). These effects were attributed to sincalide-induced vagal stimulation in that all were prevented by pretreatment with atropine or bilateral vagotomy.

11 DESCRIPTION

Sincalide for Injection is a cholecystopancreatic-gastrointestinal hormone for parenteral administration. The agent is a synthetically-prepared C-terminal octapeptide of cholecystokinin.

Each single-dose vial of sincalide provides a sterile nonpyrogenic lyophilized white to off-white cake or powder consisting of 5 mcg sincalide with 30 mg arginine hydrochloride, 15 mg lysine hydrochloride,170 mg mannitol, 4 mg methionine, 2 mg pentetic acid, and 0.04 mg sodium metabisulfite.

The pH is adjusted to 6.5 to 7.5 with hydrochloric acid and/or sodium hydroxide prior to lyophilization. Sincalide is designated chemically as L-α-aspartyl-O- sulfo-L-tyrosyl-L-methionylglycyl-L-tryptophyl-L-methionyl- L-α-aspartyl-L-phenylalaninamide.

Graphic formula:

12 CLINICAL PHARMACOLOGY

12.1 Mechanism of Action

When injected intravenously, Sincalide stimulates gallbladder contraction and reduction in size. The evacuation of bile that results is similar to that which occurs physiologically in response to endogenous cholecystokinin. Sincalide also stimulates pancreatic secretion and intestinal motility causing pyloric contraction and slows gastric emptying.

Concurrent administration of sincalide with secretin increases both the volume of pancreatic secretion and the output of bicarbonate and enzymes. This combined effect of secretin and sincalide permits the assessment of specific pancreatic function through measurement and analysis of the duodenal aspirate.

12.2 Pharmacodynamics

Following an intravenous (bolus) injection of 0.02 mcg/kg sincalide, maximal contraction of the gallbladder occurred in 5 to 15 minutes. Sincalide reduced gallbladder radiographic size by at least 40%, which is generally considered satisfactory contraction.

13 NONCLINICAL TOXICOLOGY

13.1 Carcinogenesis, Mutagenesis, Impairment of Fertility

Long-term studies in animals have not been performed to evaluate carcinogenic or mutagenic potential, or possible impairment of fertility in males or females.

16 HOW SUPPLIED/STORAGE AND HANDLING

Sincalide for Injection is supplied as 5 mcg of sincalide as a lyophilized white to off-white cake or powder for reconstitution in a single-dose vial; in packages of 5 vials (NDC 72266-248-05).

Store at 20°C to 25°C (68°F to 77°F); excursions permitted to 15°C to 30°C (59°F to 86°F) [See USP Controlled Room Temperature].

17 PATIENT COUNSELING INFORMATION

Anaphylaxis, Anaphylactic Shock and Other Serious Hypersensitivity Reactions

Inform patients serious hypersensitivity reactions, including anaphylaxis and anaphylactic shock have been reported during or following administration of Sincalide for Injection. Advise patients to report immediately to a healthcare provider if they experience symptoms of a hypersensitivity reaction [see Warnings and Precautions (5.1)].

Gastrointestinal Adverse Reactions

Advise patients that Sincalide for Injection may cause transient gastrointestinal symptoms [see Warnings and Precautions (5.3)].

Pregnancy

Advise pregnant women of the potential risk for preterm labor and spontaneous abortion [see Warnings and Precautions (5.4), Use in Specific Populations (8.1)].

Distributed by:

Fosun Pharma USA Inc.
Princeton, NJ 08540
Made in India.

1313000792-01

Principal Display Panel

Vial Label

1 Single Dose Vial NDC 72266-248-01

Sincalide for Injection

5 mcg/vial

For Intravenous Use

Carton Label

5 Single Dose Vial NDC 72266-248-05

Sincalide for Injection

5 mcg/vial

For Intravenous Use

Vial contains a sterile, lyophilized powder providing 5 mcg sincalide (see insert for inactive ingredients); pH adjusted to 6.5 to 7.5 with hydrochloric acid and/or sodium hydroxide.

Recommended Dosage: See Prescribing Information Single-Dose Vial. Discard Unused Portion.

Store at 20°C to 25°C (68°F to 77°F), excursions permitted between 15°C to 30°C (59°F to 86°F) [See USP Controlled Room Temperature]